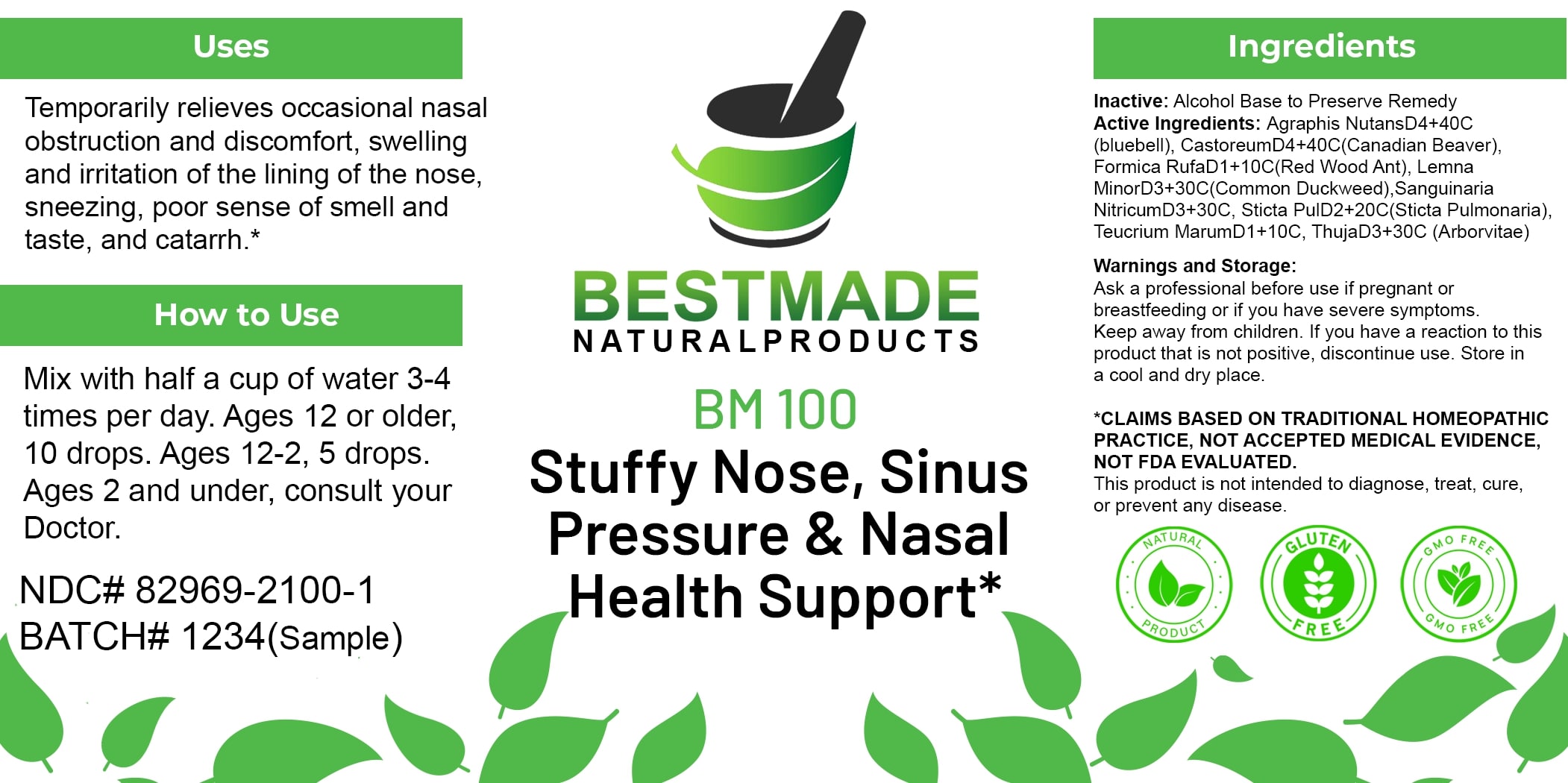 DRUG LABEL: Bestmade Natural Products BM100
NDC: 82969-2100 | Form: LIQUID
Manufacturer: Bestmade Natural Products
Category: homeopathic | Type: HUMAN OTC DRUG LABEL
Date: 20250206

ACTIVE INGREDIENTS: CASTOR CANADENSIS SCENT GLAND SECRETION 30 [hp_C]/30 [hp_C]; LEMNA MINOR 30 [hp_C]/30 [hp_C]; TEUCRIUM MARUM 30 [hp_C]/30 [hp_C]; THUJA OCCIDENTALIS LEAFY TWIG 30 [hp_C]/30 [hp_C]; HYACINTHOIDES NON-SCRIPTA 30 [hp_C]/30 [hp_C]; LOBARIA PULMONARIA 30 [hp_C]/30 [hp_C]; FORMICA RUFA 30 [hp_C]/30 [hp_C]; SANGUINARINE NITRATE 30 [hp_C]/30 [hp_C]
INACTIVE INGREDIENTS: ALCOHOL 30 [hp_C]/30 [hp_C]

BM100

DOSAGE AND ADMINISTRATION

How to Use

Mix with half a cup of water 3-4 times per day. Ages 12 or older, 10 drops. Ages 12-2, 5 drops. Ages 2 and under, consult your Doctor.

INACTIVE INGREDIENT

Ingredients

Inactive: Alcohol Base to Preserve Remedy

ACTIVE INGREDIENT

Active Ingredients: Agraphis NutansD4+40C (bluebell), CastoreumD4+40C(Canadian Beaver), Formica RufaD1+10C(Red Wood Ant), Lemna MinorD3+30C(Common Duckweed), Sanguinaria NitricumD3+30C, Sticta PulD2+20C(Sticta Pulmonaria), Teucrium MarumD1+10C, ThujaD3+30C(Arborvitae)

Uses

Temporarily relieves occasional nasal obstruction and discomfort, swelling and irritation of the lining of the nose, sneezing, poor sense of smell and taste, and catarrh.*

*CLAIMS BASED ON TRADITIONAL HOMEOPATHIC PRACTICE, NOT ACCEPTED MEDICAL EVIDENCE, NOT FDA EVALUATED. This product is not intended to diagnose, treat, cure, or prevent any disease.

Uses

Temporarily relieves occasional nasal obstruction and discomfort, swelling and irritation of the lining of the nose, sneezing, poor sense of smell and taste, and catarrh.*

*CLAIMS BASED ON TRADITIONAL HOMEOPATHIC PRACTICE, NOT ACCEPTED MEDICAL EVIDENCE, NOT FDA EVALUATED. This product is not intended to diagnose, treat, cure, or prevent any disease.

KEEP OUT OF REACH OF CHILDREN

Warnings and Storage:

Ask a professional before use if pregnant or breastfeeding or if you have severe symptoms. Keep away from children. If you have a reaction to this product that is not positive, discontinue use. Store in a cool and dry place.

Warnings and Storage:

Ask a professional before use if pregnant or breastfeeding or if you have severe symptoms. Keep away from children. If you have a reaction to this product that is not positive, discontinue use. Store in a cool and dry place.

*CLAIMS BASED ON TRADITIONAL HOMEOPATHIC PRACTICE, NOT ACCEPTED MEDICAL EVIDENCE, NOT FDA EVALUATED.

This product is not intended to diagnose, treat, cure, or prevent any disease.

Entire package label